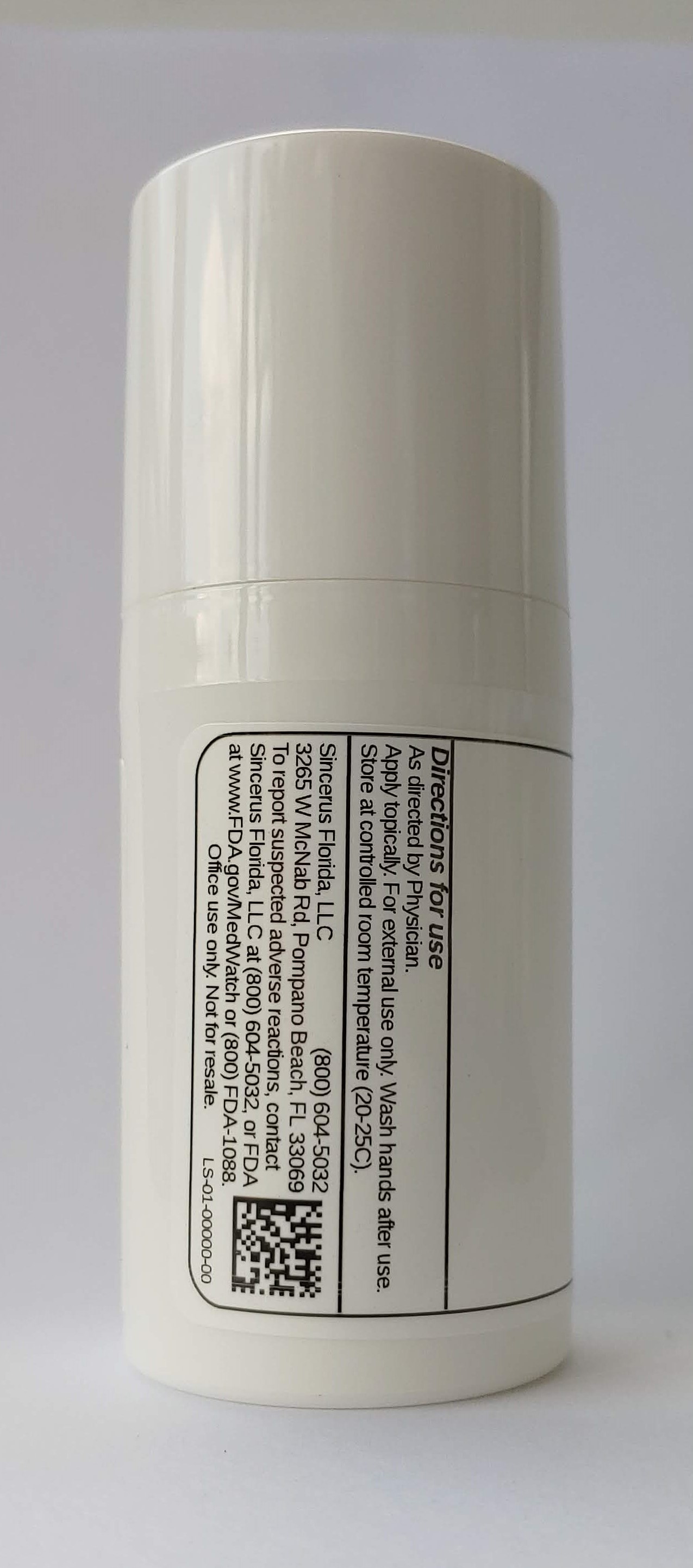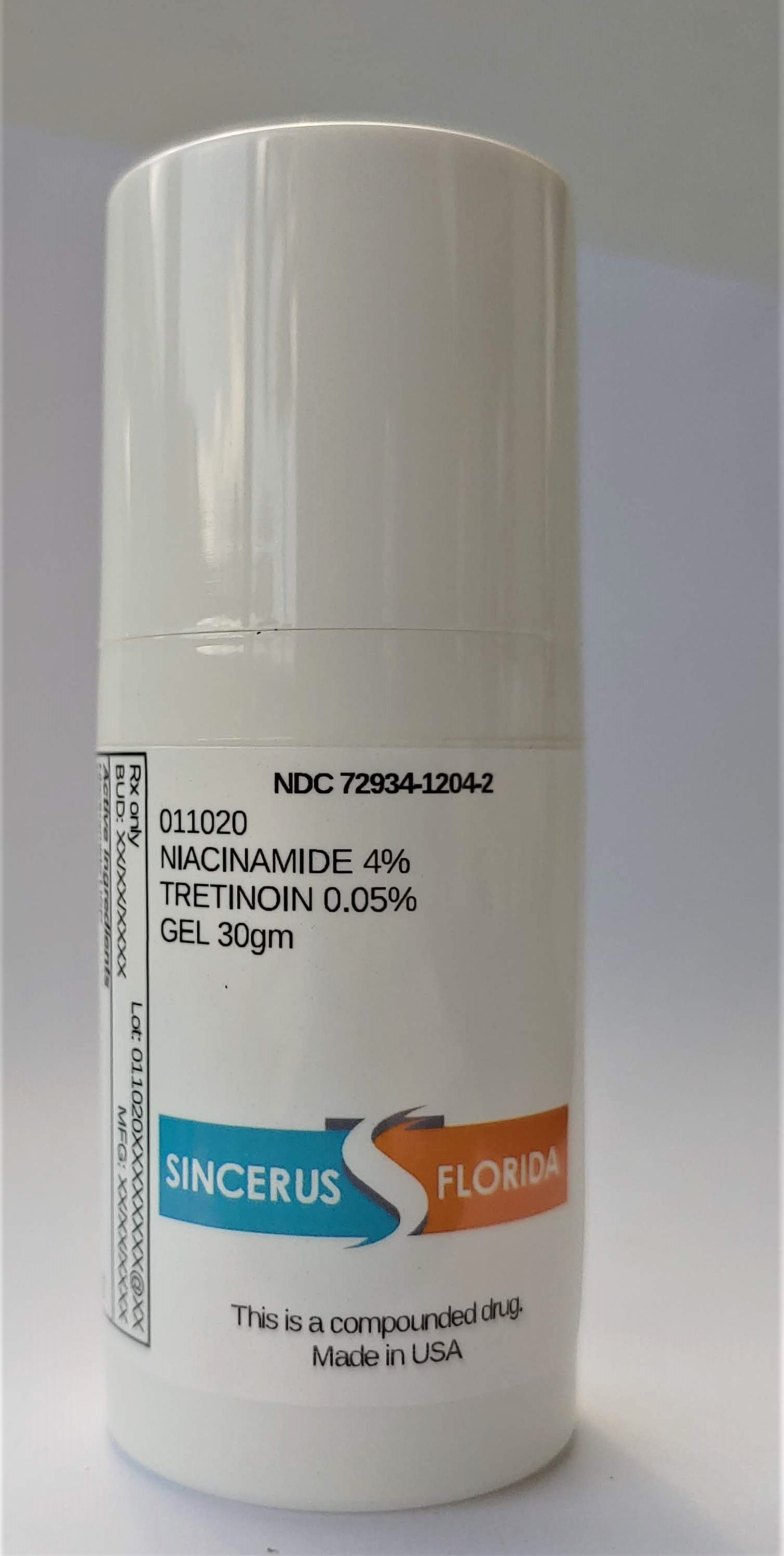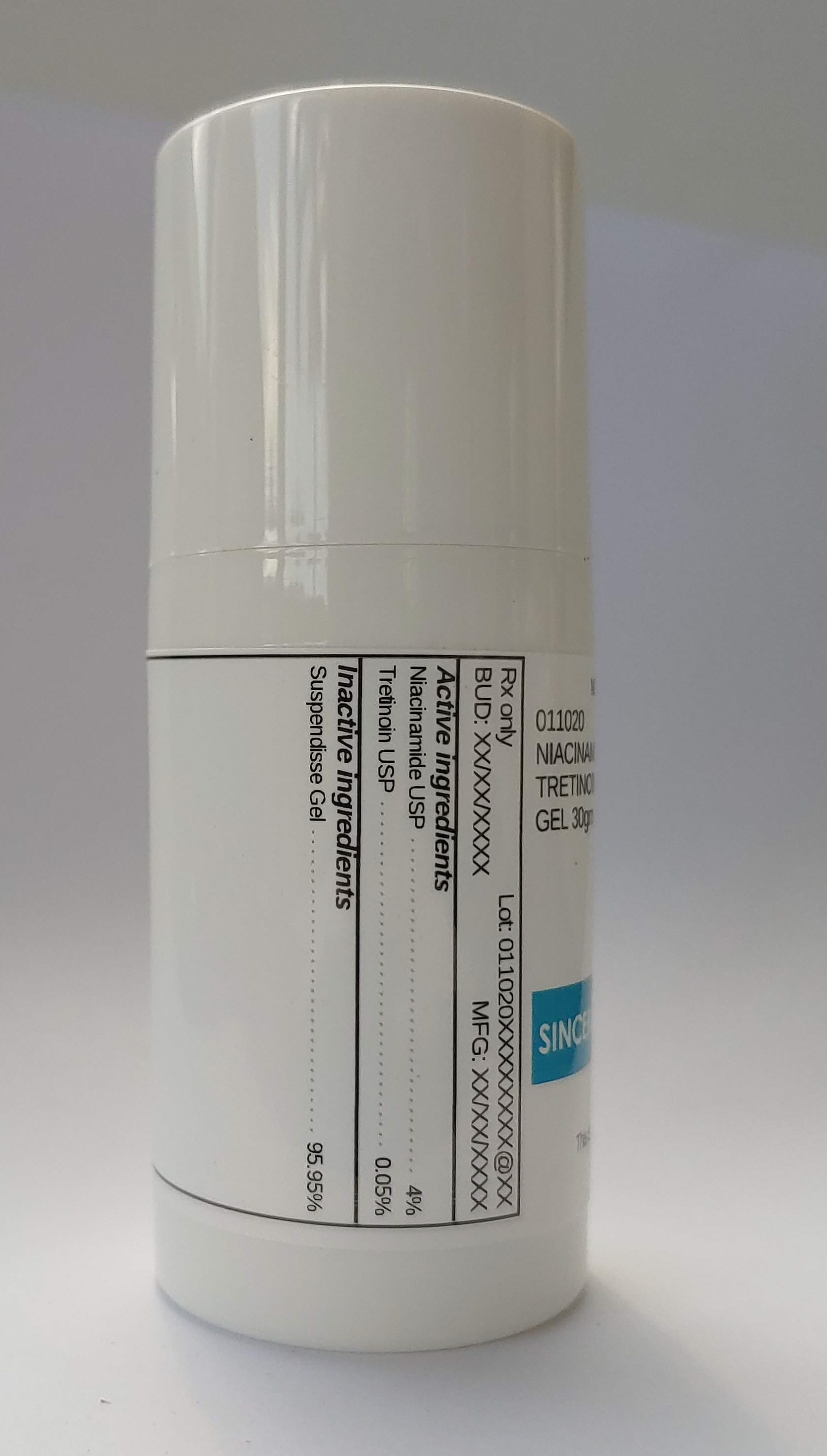 DRUG LABEL: 011020 NIACINAMIDE 4% / TRETINOIN 0.05%
NDC: 72934-1204 | Form: GEL
Manufacturer: Sincerus Florida, LLC
Category: prescription | Type: HUMAN PRESCRIPTION DRUG LABEL
Date: 20200702

ACTIVE INGREDIENTS: NIACINAMIDE 4 g/100 g; TRETINOIN 0.05 g/100 g

011020 NIACINAMIDE 4% / TRETINOIN 0.05%